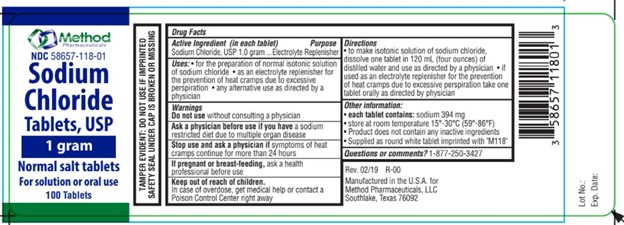 DRUG LABEL: Sodium Chloride
NDC: 58657-118 | Form: TABLET
Manufacturer: Method Pharmaceuticals
Category: otc | Type: HUMAN OTC DRUG LABEL
Date: 20251021

ACTIVE INGREDIENTS: SODIUM CHLORIDE 1 g/1 1

Sodium Chloride 1 gram

Uses

- for the normal preparation of isotonic solution of sodium chloride
- as an electrolyte replinisher for the prevention of heat cramps due to excessive perspiration
- any alternative use as directed by a physician

Indication

Electrolyte Replenisher

Ask a physician

before use if you have a sodium restricted diet due to multiple organ disease

Stop use

and ask a physician if symptoms of heat cramps continue for more than 24 hours.

If pregnant or breastfeeding,

ask a health professional before use.

Keep out of reach of children

In case of overdose, get medical help or contact a Poison Control Center right away.

Directions

- to make isotonic solutions of sodium chloride, dissolve one tablet in 120 mL (four ounces) of distilled water and use as directed by a physician.
- if used an electrolyte replinisher for the prevention of heat cramps due to excessive perspiration take one tablet orally as directed by a physician.

Warnings

Do not use without consulting a physician.

Active ingredients

Sodium Chloride

Inactive Ingredient

NONE